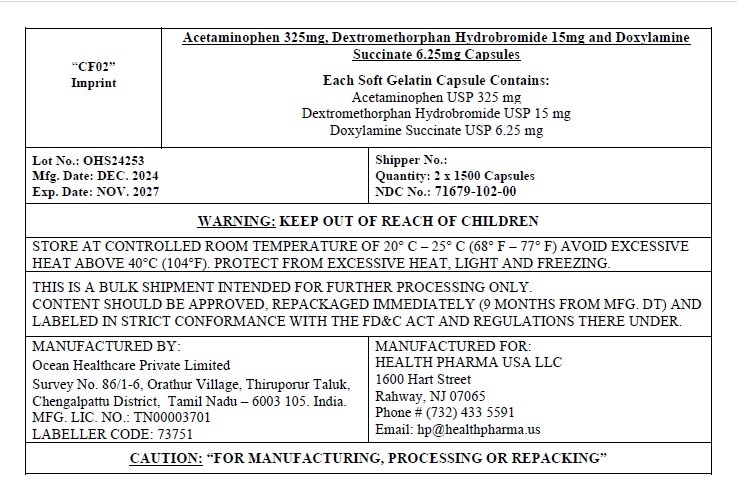 DRUG LABEL: Nighttime Cold and Flu
NDC: 71679-102 | Form: CAPSULE, LIQUID FILLED
Manufacturer: Health Pharma USA LLC
Category: otc | Type: HUMAN OTC DRUG LABEL
Date: 20250107

ACTIVE INGREDIENTS: ACETAMINOPHEN 325 mg/1 1; DEXTROMETHORPHAN HYDROBROMIDE 15 mg/1 1; DOXYLAMINE SUCCINATE 6.25 mg/1 1
INACTIVE INGREDIENTS: FD&C BLUE NO. 1; D&C YELLOW NO. 10; GELATIN; GLYCERIN; POLYETHYLENE GLYCOL 400; POVIDONE K30; PROPYLENE GLYCOL; WATER; SORBITOL SOLUTION; SORBITAN

Night-Time Cold & Flu Relief

Active ingredients (in each Softgels)

Acetaminophen 325 mg

Dextromethorphan HBr 15 mg

Doxylamine succinate 6.25 mg

Purpose

Pain reliever/Fever reducer
Cough suppressant
Antihistamine

Uses

temporarily relieves common cold/flu symptoms:

- cough due to minor throat and bronchial irritation
- sore throat
- headache
- minor aches and pains
- fever
- runny nose and sneezing

Warnings

Liver warning:This product contains acetaminophen. Severe liver damage may occur if you take

- more than 4 doses in 24 hours, which is the maximum daily amount for this product
- with other drugs containing acetaminophen
- 3 or more alcoholic drinks daily while using this product

Allergy Alert:Acetaminophen may cause severe skin reactions. Symptoms may include:

- Skin reddening
- Blisters
- Rash

If a skin reaction occurs, stop use and seek medical help right away.

Sore Throat warning:If sore throat is severe, lasts for more than 2 days, is accompanied or followed by fever, headache, rash, nausea, or vomiting, consult a doctor promptly.

Do not use

- with any other drug containing acetaminophen (prescription or nonprescription).
- if you are not sure whether a drug contains acetaminophen, ask a doctor or pharmacist.
- if you are now taking a prescription monoamine oxidase inhibitor (MAOI) (certain drugs for depression, psychiatric or emotional conditions, or Parkinson’s disease), or for 2 weeks after stopping the MAOI drug. If you do not know if your prescription drug contains an MAOI, ask a doctor or pharmacist before taking this product.

Ask a doctor before use if you have

- liver disease
- glaucoma
- cough that occurs with too much phlegm (mucus)
- a breathing problem or chronic cough that lasts or as occurs with smoking, asthma, chronic bronchitis or emphysema
- trouble urinating due to enlarged prostate gland

Ask a doctor or pharmacist before use if you are

- taking sedatives or tranquilizers
- taking the blood thinning drug warfarin

When using this product

- excitability may occur, especially in children
- marked drowsiness may occur
- avoid alcoholic drink
- be careful when driving a motor vehicle or operating machinery
- alcohol, sedatives, and tranquilizers may increase drowsiness

Stop use and ask a doctor if

- pain or cough gets worse or lasts more than 7 days
- fever gets worse or lasts more than 3 days
- redness or swelling is present
- new symptoms occur
- cough comes back or occurs with rash or headache that lasts.

These could be signs of a serious condition.

If pregnant or breast-feeding,ask a health professional before use.

Keep out of reach of children

In case of overdose, get medical help or contact a Poison Control Center right away. Quick medical attention is critical for adults as well as
for children even if you do not notice any signs or symptoms.

Direction

- take only as directed
- do not exceed 4 doses per 24 hours

adults & children 12 yrs & over | 2 softgels with water every 6 hrs
children 4 to under 12 yrs | ask a doctor
children under 4 yrs | do not use

Other information

- store at room temperature.

Inactive ingredients

D&C yellow# 10, FD&C Blue #1, Gelatin, Glycerin, Polyethylene Glycol 400, Povidone K30, Propylene Glycol, Purified Water, Sorbitol Sorbitan Solution

Questions or comments?

1-844-832-1138

M-F 9am-5pm EST

Distributed by:

Health Pharma USA LLC
Rahway, NJ 07065
www.health-Pharma.us